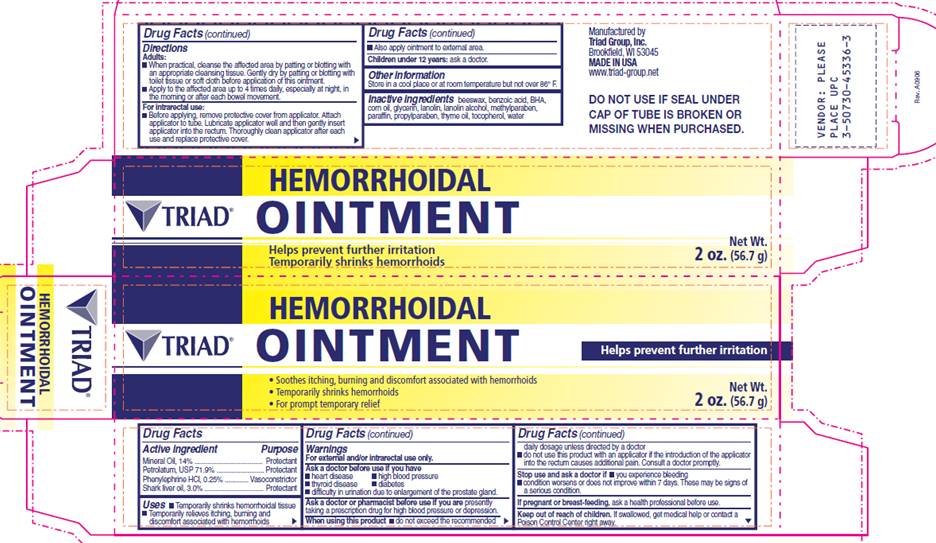 DRUG LABEL: mineral oil, petrolatum, phenylephrine hydrochloride, shark liver oil
NDC: 50730-4536 | Form: OINTMENT
Manufacturer: H and P Industries, Inc. dba Triad Group
Category: otc | Type: HUMAN OTC DRUG LABEL
Date: 20091120

ACTIVE INGREDIENTS: light mineral oil 140 mg/1 g; petrolatum 719 mg/1 g; phenylephrine hydrochloride 2.5 mg/1 g; shark liver oil 30 mg/1 g
INACTIVE INGREDIENTS: WAX, YELLOW; BENZOIC ACID; BUTYLATED HYDROXYANISOLE; CORN OIL; GLYCERIN; LANOLIN; METHYLPARABEN; PARAFFIN; PROPYLPARABEN; THYMUS OIL; .ALPHA.-TOCOPHEROL ACETATE, DL-; WATER

DRUG FACTS

ACTIVE INGREDIENTS

Mineral oil, 14%
Petrolatum, USP 71.9%

Phenylephrine HCI, 0.25%

Shark liver oil, 3.0%

PURPOSE

Protectant

Protectant

Vasoconstrictor

Protectant

USES

- Temporarily shrinks hemorrhoidal tissue
- Temporarily relieves itching, burning and discomfort associated with hemorrhoids

WARNINGS

For external and/or intrarectal use only.

Ask a doctor before use if you have

- heart disease
- thyroid disease
- high blood pressure
- diabetes
- difficulty in urination due to enlargement of the prostate gland

Ask a doctor or pharmacist before use if

you are presently taking a prescription drug for high blood pressure or depression.

When using this product

- do not exceed the recommended daily dosage.
- do not use this product with an applicator if the introduction of the applicator into the rectum causes additional pain. Consult a doctor promptly.

Stop use and ask a doctor if

- you experience bleeding
- condition worsens or does not improve within 7 days.

These may be signs of a serious condition.

If pregnant or breastfeeding

ask a health professional before use.

Keep out of reach of children

If swallowed, get medical help or contact a Poison Control Center right away.

DIRECTIONS

Adults:

- When practical, cleanse the affected area by patting or blotting with an appropriate cleansing tissue. Gently dry by patting or blotting with toilet tissue or soft cloth before application of this ointment.
- Apply to the affected area up to 4 times daily, especially at night, in the morning or after each bowel movement.

For intrarectal use:

- Before applying, remove protective cover from applicator. Attach applicator to tube. Lubricate applicator well and then gently insert applicator into the rectum. Thoroughly clean applicator after each use and replace protective cover.
- Also apply ointment to external area.

Children under 12 years: ask a doctor.

OTHER INFORMATION

Store in a cool place or at room temperature but not over 86° F.

INACTIVE INGREDIENTS

beeswax, benzoic acid, BHA, corn oil, glycerin, lanolin, lanolin alcohol, methylparaben, paraffin, propylparaben, thyme oil, tocopherol, water

PACKAGE INFORMATION

TRIAD®
HEMORRHOIDAL
OINTMENT
Helps prevent further irritation
Temporarily shrinks hemorrhoids

- Soothes itching, burning and discomfort associated with hemorrhoids
- Temporarily shrinks hemorrhoids
- For prompt temporary relief

Net wt.
2 oz. (56.7 g)
Manufactured by
Triad Group, Inc.
Brookfield, WI 53045
MADE IN USA
www.triad-group.net
DO NOT USE IF SEAL UNDER CAP OF TUBE IS BROKEN OR MISSING WHEN PURCHASED.